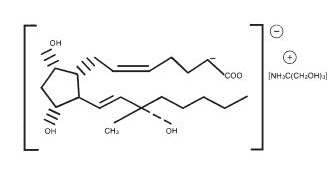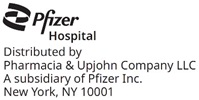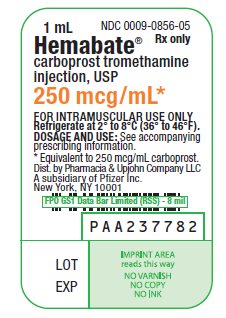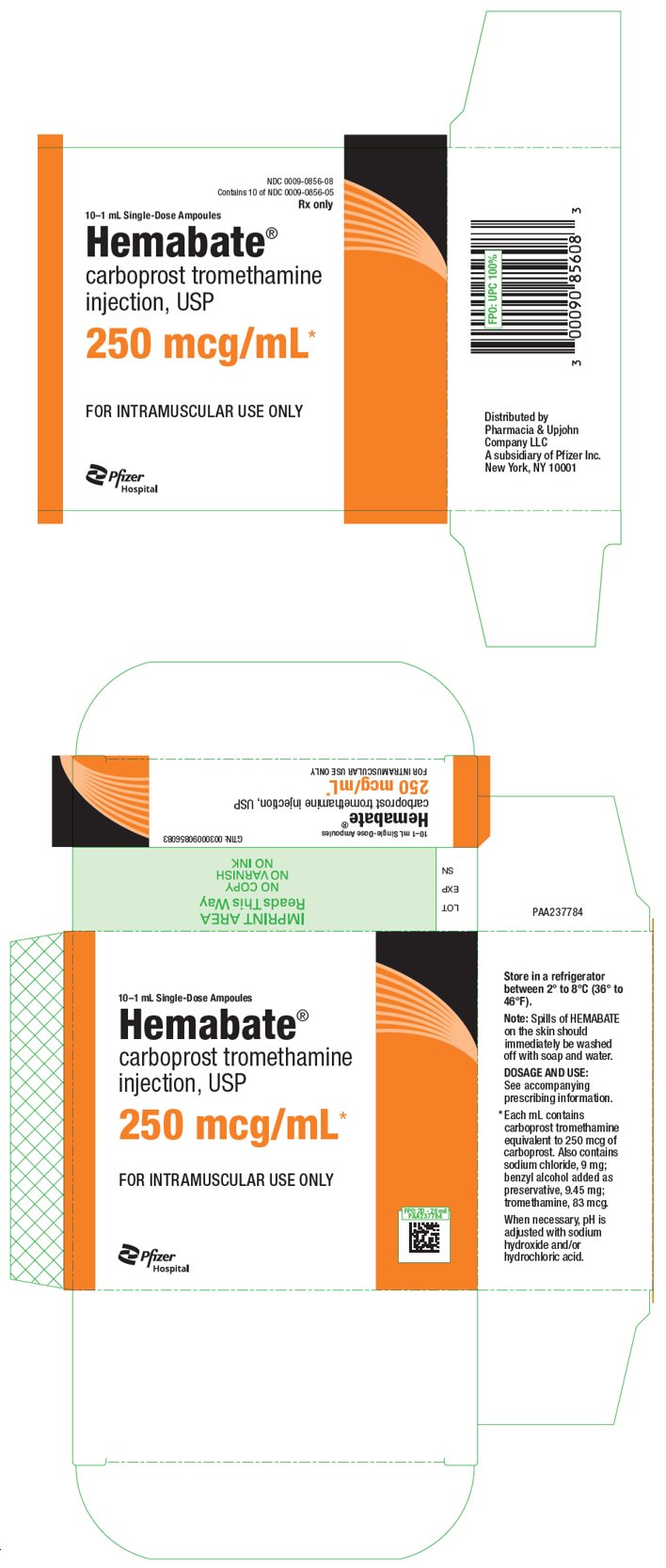 DRUG LABEL: Hemabate
NDC: 0009-0856 | Form: INJECTION, SOLUTION
Manufacturer: Pharmacia & Upjohn Company LLC
Category: prescription | Type: HUMAN PRESCRIPTION DRUG LABEL
Date: 20260128

ACTIVE INGREDIENTS: CARBOPROST TROMETHAMINE 250 ug/1 mL
INACTIVE INGREDIENTS: TROMETHAMINE 83 ug/1 mL; SODIUM CHLORIDE 9 mg/1 mL; BENZYL ALCOHOL 9.45 mg/1 mL; SODIUM HYDROXIDE; HYDROCHLORIC ACID

Hemabate®
carboprost tromethamine
injection, USP

DESCRIPTION

HEMABATE Sterile Solution, an oxytocic, contains the tromethamine salt of the (15S)-15 methyl analogue of naturally occurring prostaglandin F2α in a solution suitable for intramuscular injection.

Carboprost tromethamine is the established name for the active ingredient in HEMABATE. Four other chemical names are:

1. (15S)-15-methyl prostaglandin F2α tromethamine salt
2. 7-(3α,5α-dihydroxy-2ß-[(3S)-3-hydroxy-3-methyl-trans-1-octenyl]-1α-cyclopentyl]-cis-5-heptenoic acid compound with 2-amino-2-(hydroxymethyl)-1,3-propanediol
3. (15S)-9α,11α,15-trihydroxy-15-methylprosta-cis-5, trans-13-dienoic acid tromethamine salt
4. (15S)-15-methyl PGF2α-THAM

The structural formula is represented below:

The molecular formula is C25H47O8N. The molecular weight of carboprost tromethamine is 489.64. It is a white to slightly off-white crystalline powder. It generally melts between 95° and 105° C, depending on the rate of heating.

Carboprost tromethamine dissolves readily in water at room temperature at a concentration greater than 75 mg/mL.

HEMABATE Sterile Solution contains carboprost tromethamine equivalent to 250 mcg/mL of carboprost, and also contains tromethamine 83 mcg, sodium chloride 9 mg, and benzyl alcohol 9.45 mg added as preservative. When necessary, pH is adjusted with sodium hydroxide and/or hydrochloric acid. The solution is sterile.

CLINICAL PHARMACOLOGY

Carboprost tromethamine administered intramuscularly stimulates in the gravid uterus myometrial contractions similar to labor contractions at the end of a full term pregnancy. Whether or not these contractions result from a direct effect of carboprost on the myometrium has not been determined. Nonetheless, they evacuate the products of conception from the uterus in most cases.

Postpartum, the resultant myometrial contractions provide hemostasis at the site of placentation.

Carboprost tromethamine also stimulates the smooth muscle of the human gastrointestinal tract. This activity may produce the vomiting or diarrhea or both that is common when carboprost tromethamine is used to terminate pregnancy and for use postpartum. In laboratory animals and also in humans carboprost tromethamine can elevate body temperature. With the clinical doses of carboprost tromethamine used for the termination of pregnancy, and for use postpartum, some patients do experience transient temperature increases.

In laboratory animals and in humans large doses of carboprost tromethamine can raise blood pressure, probably by contracting the vascular smooth muscle. With the doses of carboprost tromethamine used for terminating pregnancy, this effect has not been clinically significant. In laboratory animals and also in humans carboprost tromethamine can elevate body temperature. With the clinical doses of carboprost tromethamine used for the termination of pregnancy, some patients do experience temperature increases. In some patients, carboprost tromethamine may cause transient bronchoconstriction.

Drug plasma concentrations were determined by radioimmunoassay in peripheral blood samples collected by different investigators from 10 patients undergoing abortion. The patients had been injected intramuscularly with 250 micrograms of carboprost at two hour intervals. Blood levels of drug peaked at an average of 2060 picograms/mL one-half hour after the first injection then declined to an average concentration of 770 picograms/mL two hours after the first injection just before the second injection. The average plasma concentration one-half hour after the second injection was slightly higher (2663 picograms/mL) than that after the first injection and decreased again to an average of 1047 picograms/mL by two hours after the second injection. Plasma samples were collected from 5 of these 10 patients following additional injections of the prostaglandin. The average peak concentrations of drug were slightly higher following each successive injection of the prostaglandin, but always decreased to levels less than the preceding peak values by two hours after each injection.

Five women who had delivery spontaneously at term were treated immediately postpartum with a single injection of 250 micrograms of carboprost tromethamine. Peripheral blood samples were collected at several times during the four hours following treatment and carboprost tromethamine levels were determined by radioimmunoassay. The highest concentration of carboprost tromethamine was observed at 15 minutes in two patients (3009 and 2916 picograms/mL), at 30 minutes in two patients (3097 and 2792 picograms/mL), and at 60 minutes in one patient (2718 picograms/mL).

INDICATIONS AND USAGE

HEMABATE Sterile Solution is indicated for aborting pregnancy between the 13th and 20th weeks of gestation as calculated from the first day of the last normal menstrual period and in the following conditions related to second trimester abortion:

1. Failure of expulsion of the fetus during the course of treatment by another method;
2. Premature rupture of membranes in intrauterine methods with loss of drug and insufficient or absent uterine activity;
3. Requirement of a repeat intrauterine instillation of drug for expulsion of the fetus;
4. Inadvertent or spontaneous rupture of membranes in the presence of a previable fetus and absence of adequate activity for expulsion.

HEMABATE is indicated for the treatment of postpartum hemorrhage due to uterine atony which has not responded to conventional methods of management. Prior treatment should include the use of intravenously administered oxytocin, manipulative techniques such as uterine massage and, unless contraindicated, intramuscular ergot preparations. Studies have shown that in such cases, the use of HEMABATE has resulted in satisfactory control of hemorrhage, although it is unclear whether or not ongoing or delayed effects of previously administered ecbolic agents have contributed to the outcome. In a high proportion of cases, HEMABATE used in this manner has resulted in the cessation of life threatening bleeding and the avoidance of emergency surgical intervention.

CONTRAINDICATIONS

1. Hypersensitivity (including anaphylaxis and angioedema) to HEMABATE Sterile Solution [see ADVERSE REACTIONS, Post-marketing Experience]
2. Acute pelvic inflammatory disease
3. Patients with active cardiac, pulmonary, renal or hepatic disease

WARNINGS

WARNINGS

HEMABATE Sterile Solution (carboprost tromethamine), like other potent oxytocic agents, should be used only with strict adherence to recommended dosages.

HEMABATE should be used by medically trained personnel in a hospital which can provide immediate intensive care and acute surgical facilities.

HEMABATE does not appear to directly affect the fetoplacental unit. Therefore, the possibility does exist that the previable fetus aborted by HEMABATE could exhibit transient life signs. HEMABATE is not indicated if the fetus in utero has reached the stage of viability. HEMABATE should not be considered a feticidal agent.

TERATOGENIC EFFECTS

Evidence from animal studies has suggested that certain other prostaglandins have some teratogenic potential. Although these studies do not indicate that HEMABATE is teratogenic, any pregnancy termination with HEMABATE that fails should be completed by some other means.

This product contains benzyl alcohol. Benzyl alcohol has been reported to be associated with a fatal "Gasping Syndrome" in premature infants.

PRECAUTIONS

General

Animal studies lasting several weeks at high doses have shown that prostaglandins of the E and F series can induce proliferation of bone. Such effects have also been noted in newborn infants who have received prostaglandin E1 during prolonged treatment. There is no evidence that short term administration of HEMABATE Sterile Solution can cause similar bone effects.

In patients with a history of asthma, hypo- or hypertension, cardiovascular, renal, or hepatic disease, anemia, jaundice, diabetes, or epilepsy, HEMABATE should be used cautiously.

As with any oxytocic agent, HEMABATE should be used with caution in patients with compromised (scarred) uteri.

Abortion

As with spontaneous abortion, a process which is sometimes incomplete, abortion induced by HEMABATE may be expected to be incomplete in about 20% of cases.

Although the incidence of cervical trauma is extremely small, the cervix should always be carefully examined immediately post-abortion.

Use of HEMABATE is associated with transient pyrexia that may be due to its effect on hypothalamic thermoregulation. Temperature elevations exceeding 2° F (1.1° C) were observed in approximately one-eighth of the patients who received the recommended dosage regimen. In all cases, temperature returned to normal when therapy ended. Differentiation of post-abortion endometritis from drug-induced temperature elevations is difficult, but with increasing clinical experience, the distinctions become more obvious and are summarized below:

 | Endometritis pyrexia |  | Pyrexia induced by HEMABATE
1. | Time of onset: Typically, on third post-abortional day (38° C or higher). |  | Within 1 to 16 hours after the first injection.
2. | Duration: Untreated pyrexia and infection continue and may give rise to other pelvic infections. |  | Temperatures revert to pretreatment levels after discontinuation of therapy without any other treatment.
3. | Retention: Products of conception are often retained in the cervical os or uterine cavity. |  | Temperature elevation occurs whether or not tissue is retained.
4. | Histology: Endometrium is infiltrated with lymphocytes and some areas are necrotic and hemorrhagic. |  | Although the endometrial stroma may be edematous and vascular, it is not inflamed.
5. | The uterus: Often remains boggy and soft with tenderness over the fundus, and pain on moving the cervix on bimanual examination. |  | Uterine involution normal and uterus is not tender.
6. | Discharge: Often associated with foul-smelling lochia and leukorrhea. |  | Lochia normal.
7. | Cervical culture: The culture of pathological organisms from the cervix or uterine cavity after abortion alone does not warrant the diagnosis of septic abortion in the absence of clinical evidence of sepsis. Pathogens have been cultured soon after abortion in patients with no infections. Persistent positive culture with clear clinical signs of infections are significant in the differential diagnosis.
8. | Blood count: Leukocytosis and differential white cell counts do not distinguish between endometritis and hyperthermia caused by HEMABATE since total WBC's may increase during infection and transient leukocytosis may also be drug-induced. Fluids should be forced in patients with drug-induced fever and no clinical or bacteriological evidence of intrauterine infection. Any other simple empirical measures for temperature reduction are unnecessary because all fevers induced by HEMABATE have been transient or self-limiting.

Postpartum Hemorrhage

Increased blood pressure. In the postpartum hemorrhage series, 5/115 (4%) of patients had an increase of blood pressure reported as a side effect. The degree of hypertension was moderate and it is not certain as to whether this was in fact due to a direct effect of HEMABATE or a return to a status of pregnancy associated hypertension manifest by the correction of hypovolemic shock. In any event the cases reported did not require specific therapy for the elevated blood pressure.

Use in patients with chorioamnionitis. During the clinical trials with HEMABATE, chorioamnionitis was identified as a complication contributing to postpartum uterine atony and hemorrhage in 8/115 (7%) of cases, 3 of which failed to respond to HEMABATE. This complication during labor may have an inhibitory effect on the uterine response to HEMABATE similar to what has been reported for other oxytocic agents. [Duff, Sanders, and Gibbs; The course of labor in term patients with chorioamnionitis; Am. J. Obstet. Gynecol.; vol. 147, no. 4, October 15, 1983 pp 391–395.]

Drug Interactions

HEMABATE may augment the activity of other oxytocic agents. Concomitant use with other oxytocic agents is not recommended.

Carcinogenesis, Mutagenesis, Impairment of Fertility

Carcinogenic bioassay studies have not been conducted in animals with HEMABATE due to the limited indications for use and short duration of administration. No evidence of mutagenicity was observed in the Micronucleus Test or Ames Assay.

Pregnancy

Teratogenic Effects

Animal studies do not indicate that HEMABATE is teratogenic, however, it has been shown to be embryotoxic in rats and rabbits and any dose which produces increased uterine tone could put the embryo or fetus at risk.

Pediatric Use

Safety and effectiveness in pediatric patients have not been established.

ADVERSE REACTIONS

The adverse effects of HEMABATE Sterile Solution are generally transient and reversible when therapy ends. The most frequent adverse reactions observed are related to its contractile effect on smooth muscle.

In patients studied, approximately two-thirds experienced vomiting and diarrhea, approximately one-third had nausea, one-eighth had a temperature increase greater than 2° F, and one-fourteenth experienced flushing.

The pretreatment or concurrent administration of antiemetic and antidiarrheal drugs decreases considerably the very high incidence of gastrointestinal effects common with all prostaglandins used for abortion. Their use should be considered an integral part of the management of patients undergoing abortion with HEMABATE.

Of those patients experiencing a temperature elevation, approximately one-sixteenth had a clinical diagnosis of endometritis. The remaining temperature elevations returned to normal within several hours after the last injection.

Adverse effects observed during the use of HEMABATE for abortion and for hemorrhage, not all of which are clearly drug related, in decreasing order of frequency include:

Vomiting | Nervousness
Diarrhea | Nosebleed
Nausea | Sleep disorders
Flushing or hot flashes | Dyspnea
Chills or shivering | Tightness in chest
Coughing | Wheezing
Headaches | Posterior cervical perforation
Endometritis | Weakness
Hiccough | Diaphoresis
Dysmenorrhea-like pain | Dizziness
Paresthesia | Blurred vision
Backache | Epigastric pain
Muscular pain | Excessive thirst
Breast tenderness | Twitching eyelids
Eye pain | Gagging, retching
Drowsiness | Dry throat
Dystonia | Sensation of choking
Asthma | Thyroid storm
Injection site pain | Syncope
Tinnitus | Palpitations
Vertigo | Rash
Vaso-vagal syndrome | Upper respiratory infection
Dryness of mouth | Leg cramps
Hyperventilation | Perforated uterus
Respiratory distress | Anxiety
Hematemesis | Chest pain
Taste alterations | Retained placental fragment
Urinary tract infection | Shortness of breath
Septic shock | Fullness of throat
Torticollis | Uterine sacculation
Lethargy | Faintness, light-headedness
Hypertension | Uterine rupture
Tachycardia
Pulmonary edema
Endometritis from IUCD

The most common complications when HEMABATE was utilized for abortion requiring additional treatment after discharge from the hospital were endometritis, retained placental fragments, and excessive uterine bleeding, occurring in about one in every 50 patients.

Post-marketing experience

Hypersensitivity reactions (e.g. Anaphylactic reaction, Anaphylactic shock, Anaphylactoid reaction, Angioedema).

DOSAGE AND ADMINISTRATION

1. Abortion and Indications 1–4

An initial dose of 1 mL of HEMABATE Sterile Solution (containing the equivalent of 250 micrograms of carboprost) is to be administered deep in the muscle with a tuberculin syringe. Subsequent doses of 250 micrograms should be administered at 1½ to 3½ hour intervals depending on uterine response.

An optional test dose of 100 micrograms (0.4 mL) may be administered initially. The dose may be increased to 500 micrograms (2 mL) if uterine contractility is judged to be inadequate after several doses of 250 micrograms (1 mL).

The total dose administered of carboprost tromethamine should not exceed 12 milligrams and continuous administration of the drug for more than two days is not recommended.

2. For Refractory Postpartum Uterine Bleeding

An initial dose of 250 micrograms of HEMABATE Sterile Solution (1 mL of HEMABATE) is to be given deep, intramuscularly. In clinical trials it was found that the majority of successful cases (73%) responded to single injections. In some selected cases, however, multiple dosing at intervals of 15 to 90 minutes was carried out with successful outcome. The need for additional injections and the interval at which these should be given can be determined only by the attending physicians as dictated by the course of clinical events. The total dose of HEMABATE should not exceed 2 milligrams (8 doses).

Parenteral drug products should be inspected visually for particulate matter and discoloration prior to administration, whenever solution and container permit.

HOW SUPPLIED

HEMABATE Sterile Solution is available in the following packages:

1 mL ampoules | NDC 0009-0856-05
10 × 1 mL ampoules | NDC 0009-0856-08

HEMABATE contains carboprost tromethamine equivalent to 250 mcg/mL of carboprost.

STORAGE AND HANDLING

HEMABATE must be refrigerated at 2° to 8° C (36° to 46° F).

This product's label may have been updated. For current full prescribing information, please visit www.pfizer.com

Rx only

LAB-0032-10.0
Revised March 2025

PRINCIPAL DISPLAY PANEL - 1 mL Ampule Label

1 mL

NDC 0009-0856-05
Rx only

Hemabate®
carboprost tromethamine
injection, USP

250 mcg/mL*

FOR INTRAMUSCULAR USE ONLY
Refrigerate at 2° to 8°C (36° to 46°F).
DOSAGE AND USE: See accompanying
prescribing information.
* Equivalent to 250 mcg carboprost.
Dist. by Pharmacia & Upjohn Company LLC
A subsidiary of Pfizer Inc.
New York, NY 10001

PAA237782

LOT
EXP

PRINCIPAL DISPLAY PANEL - 10 Single-Dose Ampoule Carton

NDC 0009-0856-08
Contains 10 of NDC 0009-0856-05

Rx only

10–1 mL Single-Dose Ampoules

Hemabate®
carboprost tromethamine
injection, USP

250 mcg/mL*

FOR INTRAMUSCULAR USE ONLY

Pfizer
Hospital